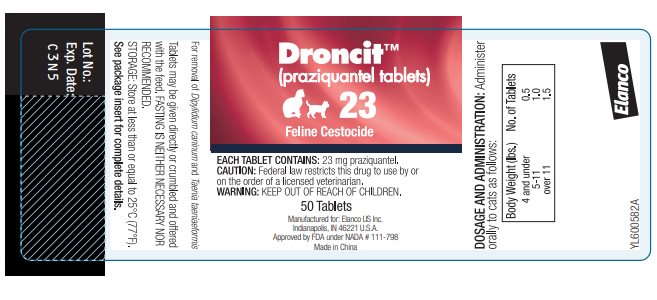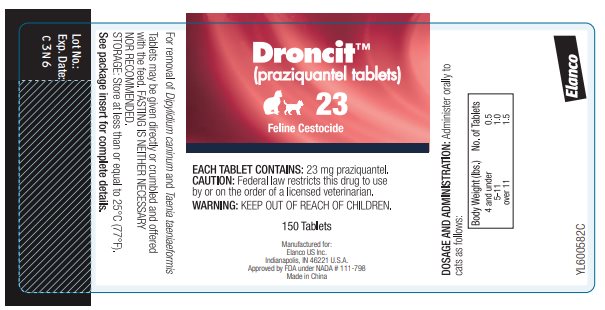 DRUG LABEL: Droncit Feline Cestocide
NDC: 58198-0032 | Form: TABLET
Manufacturer: Elanco US Inc.
Category: animal | Type: PRESCRIPTION ANIMAL DRUG LABEL
Date: 20260223

ACTIVE INGREDIENTS: PRAZIQUANTEL 23 mg/1 1

Elanco
DroncitTM
(praziquantel tablets)
23 Feline Cestocide

CAUTION: Federal law restricts this drug to use by or on the order of a licensed veterinarian.

Each Tablet Contains 23 mg Praziquantel

DESCRIPTION:

Droncit (praziquantel tablets) 23 Feline Cestocide are sized for easy oral administration to either adult cats or kittens. The tablets may be crumbled and mixed with the feed.

INDICATIONS:

Droncit (praziquantel tablets) 23 Feline Cestocide are indicated for the removal of the following feline cestodes: Dipylidium caninum and Taenia taeniaeformis.

CONTRAINDICATIONS:

There are no known contraindications to the use of praziquantel in cats.

ACTION:

Droncit (praziquantel tablets) is absorbed, metabolized in the liver and excreted in the bile. Upon entering the digestive tract from the bile, cestocidal activity is exhibited.^1

Following exposure to praziquantel, the tapeworm loses its ability to resist digestion by the mammalian host. Because of this, whole tapeworms, including the scolex, are very rarely passed after administration of praziquantel. In many instances only disintegrated and partially digested pieces of tapeworms will be seen in the stool. The majority of tapeworms killed are digested and are not found in the feces.

USE DIRECTIONS:

Droncit (praziquantel tablets) 23 Feline Cestocide may be administered directly per os or crumbled and mixed with the feed. The recommended dosage of praziquantel varies according to body weight. Smaller animals require a relatively larger dosage because of their higher metabolic rate. The optimum dose for each individual animal will be achieved by utilizing the following dosage schedule:

Cats and Kittens*
4 pounds and under | ½ tablet
5-11 pounds | 1 tablet
Over 11 pounds | 1 ½ tablets
*Not intended for use in kittens less than 6 weeks of age.

FASTING:

The recommended dosage of praziquantel is not affected by the presence or absence of food in the gastrointestinal tract, therefore, FASTING IS NEITHER NECESSARY NOR RECOMMENDED.

RETREATMENT:

For those animals maintained on premises where reinfections are likely to occur, clients should be instructed in the steps necessary to prevent reinfection; otherwise, retreatment may be necessary. This is especially true in cases of Dipylidium caninum infections where reinfection is almost certain to occur if fleas are not removed from the animal and its environment.

ANIMAL SAFETY:

The safety index has been derived from controlled safety evaluations, clinical trials and prior approved use in foreign countries.

Dosages of 5 times the labeled rate at 14 day intervals to cats as young as 5½ weeks did not produce clinical signs of toxicity. No significant clinical chemistry, hematological, or histopathological changes occurred. Symptoms of gross overdosage include vomition, salivation, diarrhea and depression.

PREGNANCY:

Droncit (praziquantel tablets) has been tested in breeding and pregnant cats. No adverse effects were noted.

ADVERSE REACTIONS:

One instance of diarrhea and one of salivation (1.5%) were reported during the field trials in which 135 cats were administered Droncit (praziquantel tablets) 23 Feline Cestocide.

CONTACT INFORMATION:

For product questions, to report adverse reactions, or for a copy of the Safety Data Sheet (SDS), call Elanco Product & Veterinary Support at 888-545-5973.

For additional information about reporting adverse drug experiences for animal drugs, contact FDA at 1-888-FDA-VETS or http://www.fda.gov/reportanimalae.

WARNING:

Keep out of the reach of children. Not for human use.

STORAGE:

Store at less than or equal to 25ºC (77ºF)

HOW SUPPLIED:

Bottle of 50 and 150 scored tablets.

Each scored tablet contains 23 mg praziquantel.

— 50 Tablets

—150 Tablets

REFERENCES:

1. Andrews, P. Pharmacokinetic Studies with Droncit in Animals Using a Biological Assay. Veterinary Medical Review 2/76: 154-165.

Manufactured for:
Elanco US Inc.
Indianapolis, IN 46221 U.S.A.

Droncit, Elanco and the diagonal bar logo are trademarks of Elanco or its affiliates.

© 2026 Elanco or its affiliates

Approved by FDA under NADA # 111-798

PA600582X

Revised: November 2025

Elanco™

Principal Display Panel

DroncitTM

(praziquantel tablets)

23

Feline Cestocide

EACH TABLET CONTAINS: 23 mg praziquantel.

CAUTION: Federal law restricts this drug to use by or
on the order of a licensed veterinarian.

WARNING: KEEP OUT OF REACH OF CHILDREN.

50 Tablets

Manufactured for: Elanco US Inc.
Indianapolis, IN 46221 U.S.A.
Approved by FDA under NADA # 111-798
Made in China

DroncitTM

(praziquantel tablets)

23

Feline Cestocide

EACH TABLET CONTAINS: 23 mg praziquantel.

CAUTION: Federal law restricts this drug to use
by or on the order of a licensed veterinarian.

WARNING: KEEP OUT OF REACH OF CHILDREN.

150 Tablets

Manufactured for:
Elanco US Inc.
Indianapolis, IN 46221 U.S.A.
Approved by FDA under NADA # 111-798
Made in China